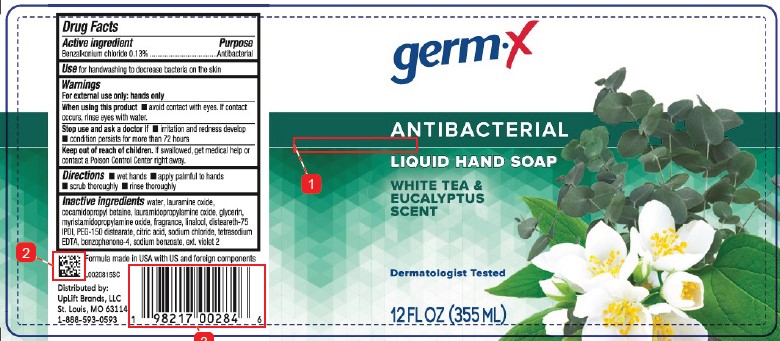 DRUG LABEL: Antibacterial Hand White Tea and Eucalyptus
NDC: 83986-140 | Form: SOAP
Manufacturer: UpLift Brands LLC
Category: otc | Type: HUMAN OTC DRUG LABEL
Date: 20260202

ACTIVE INGREDIENTS: BENZALKONIUM CHLORIDE 1.3 mg/1 mL
INACTIVE INGREDIENTS: WATER; LAURAMINE OXIDE; COCAMIDOPROPYL BETAINE; LAURAMIDOPROPYLAMINE OXIDE; GLYCERIN; MYRISTAMIDOPROPYLAMINE OXIDE; LINALOOL, (+/-)-; DISTEARETH-75 ISOPHORONE DIISOCYANATE; PEG-150 DISTEARATE; CITRIC ACID MONOHYDRATE; SODIUM CHLORIDE; EDETATE SODIUM; SULISOBENZONE; SODIUM BENZOATE; EXT. D&C VIOLET NO. 2

Germ-X D14.002/D14AC
Antibacterial Hand White Tea and Eucalyptus

Active Ingredient

Benzalkonium chloride 0.13%

Purpose

Antibacterial

Use

for handwashing to decrease bacteria on the skin

Warnings

For external use only: hands only

When using this product

- avoid contact with eyes. If contact occurs, rinse eyes with water.

Stop use and ask a doctor if

- irritation and redness develop
- condition persists for more than 72 hours

Keep out of reach of children.

If swallowed, get medical help or contact a Poison Control Center right away.

Directions

- wet hands
- apply palmful to hands
- scrub thoroughly
- rinse thoroughly

Inactive Ingredients

water, lauramine oxide, cocamidopropyl betaine, lauramidopropylamine oxide, glycerin, myristamidopropylamine oxide, fragrance, linalool, disteareth-75 IPDI, PEG-150 distearate, citric acid, sodium chloride, tetrasodium EDTA, benzophenone-4, sodium benzoate, ext. violet 2

Adverse reaction

Formula made in USA with US and foreign components.

Distributed by: UpLift Brands, LLC

St. Louis, MO 63114

1-888-593-0593

Principal Panel Display

germ-x

ANTIBACTERIAL

LIQUID HAND SOAP

WHITE TEA & EUCALYPTUS SCENT

Dermatologist Tested

12 FL OZ (355 mL)